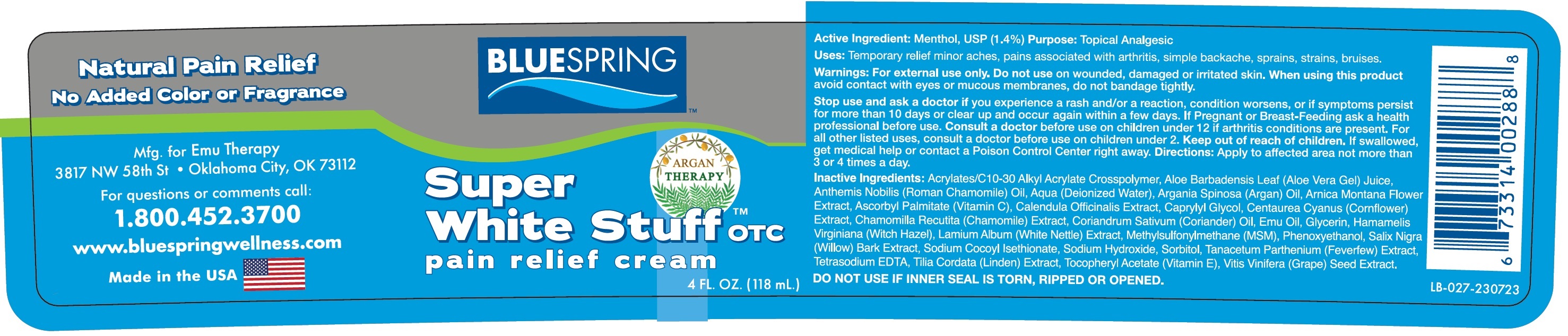 DRUG LABEL: SUPER WHITE STUFF Pain Relief
NDC: 14448-445 | Form: CREAM
Manufacturer: BLUE SPRING WELLNESS
Category: otc | Type: HUMAN OTC DRUG LABEL
Date: 20240123

ACTIVE INGREDIENTS: MENTHOL 14 mg/1 mL
INACTIVE INGREDIENTS: ALOE VERA LEAF; WATER; ARGAN OIL; ARNICA MONTANA FLOWER; ASCORBYL PALMITATE; CALENDULA OFFICINALIS FLOWER; CAPRYLYL GLYCOL; CHAMOMILE; CORIANDER; EMU OIL; GLYCERIN; WITCH HAZEL; DIMETHYL SULFONE; PHENOXYETHANOL; SALIX NIGRA BARK; SODIUM COCOYL ISETHIONATE; SODIUM HYDROXIDE; SORBITOL; FEVERFEW; EDETATE SODIUM; TILIA CORDATA WHOLE; .ALPHA.-TOCOPHEROL ACETATE; VITIS VINIFERA SEED

SUPER WHITE STUFF Pain Relief Cream

Active Ingredient:

Menthol, USP (1.4%)

Purpose:

Topical Analgesic

Uses:

Temporary relief minor aches, pains associated with arthritis, simple backache, sprains, strains, bruises.

Warnings:

For external use only.

Do not use

on wounded, damaged or irritated skin.

When using this product

avoid contact with eyes or mucous membranes, do not bandage tightly.

Stop use and ask a doctor if

you experience a rash and/or a reaction, condition worsens, or if symptoms persist for more than 10 days or clear up and occur again within few days.

If Pregnant or Breast-Feeding

ask a health professional before use. Consult a doctorbefore use on children under 12 if arthritis conditions are present. For all other listed uses, consult a doctor before use on children under 2.

Keep out of reach of children.

If swallowed, get medical help or contact a Posion Control Center right away.

Directions:

Apply to affected area not more than 3 or 4 times a day.

Inactive Ingredients:

Acrylates/C10-30 Alkyl Acrylate Crosspolymer, Aloe Barbadensis Leaf (Aloe Vera Gel) Juice, Anthemis Nobilis (Roman Chamomile) Oil, Aqua (Deionized Water), Argania Spinosa (Argan) Oil, Arnica Montana Flower Extract, Ascorbyl Palmitate (Vitamin C), Calendula Officinalis Extract, Caprylyl Glycol, Centaurea Cyanus (Cornflower) Extract, Chamomilla Recutita (Chamomile) Extract, Coriandrum Sativum (Coriander) Oil, Emu Oil, Glycerin, Hamamelis Virginiana (Witch Hazel), Lamium Album (White Nettle) Extract, Methylsulfonylmethane (MSM), Phenoxyethanol, Salix Nigra (Willow) Bark Extract, Sodium Cocoyl Isethionate, Sodium Hydroxide, Sorbitol, Tanacetum Parthenium (Feverfew) Extract, Tetrasodium EDTA, Tilia Cordata (Linden) Extract, Tocopheryl Acetate (Vitamin E), Vitis Vinifera (Grape) Seed Extract.